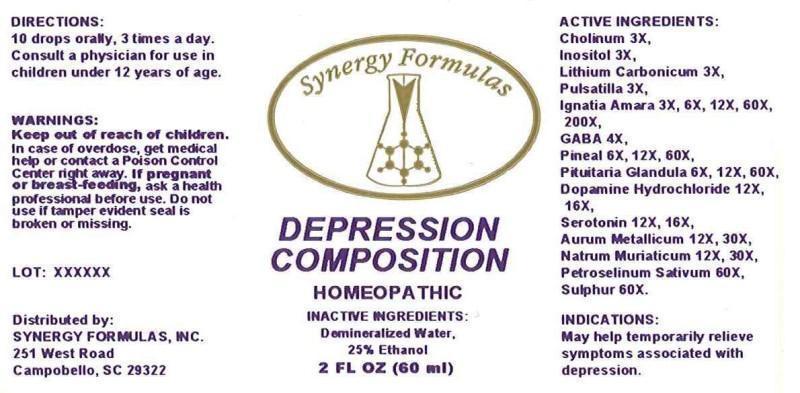 DRUG LABEL: DEPRESSION COMPOSITION
NDC: 43772-0043 | Form: LIQUID
Manufacturer: Synergy Formulas, Inc.
Category: homeopathic | Type: HUMAN OTC DRUG LABEL
Date: 20140926

ACTIVE INGREDIENTS: CHOLINE HYDROXIDE 3 [hp_X]/1 mL; INOSITOL 3 [hp_X]/1 mL; LITHIUM CARBONATE 3 [hp_X]/1 mL; PULSATILLA VULGARIS 3 [hp_X]/1 mL; STRYCHNOS IGNATII SEED 3 [hp_X]/1 mL; .GAMMA.-AMINOBUTYRIC ACID 4 [hp_X]/1 mL; SUS SCROFA PINEAL GLAND 6 [hp_X]/1 mL; SUS SCROFA PITUITARY GLAND 6 [hp_X]/1 mL; DOPAMINE HYDROCHLORIDE 12 [hp_X]/1 mL; SEROTONIN HYDROCHLORIDE 12 [hp_X]/1 mL; GOLD 12 [hp_X]/1 mL; SODIUM CHLORIDE 12 [hp_X]/1 mL; PETROSELINUM CRISPUM 60 [hp_X]/1 mL; SULFUR 60 [hp_X]/1 mL
INACTIVE INGREDIENTS: WATER; ALCOHOL

DRUG FACTS

ACTIVE INGREDIENTS:

CHOLINUM 3X, INOSITOL 3X, LITHIUM CARBONICUM 3X, PULSATILLA (VULGARIS) 3X, IGNATIA AMARA 3X, 6X, 12X, 60X, 200X, GABA (GAMMA-AMNIOBUTYRIC ACID) 4X, PINEAL (SUIS) 6X, 12X, 60X, PITUITARIA GLANDULA (SUIS) 6X, 12X, 60X, DOPAMINE HYDROCHLORIDE 12X, 16X, SEROTONIN (HYDROCHLORIDE) 12X, 16X, AURUM METALLICUM 12X, 30X, NATRUM MURIATICUM 12X, 30X, PETROSELINUM SATIVUM 60X, SULPHUR 60X

INDICATIONS:

May help temporarily relieve symptoms associated with depression.

WARNINGS:

Keep out of reach of children. In case of overdose, get medical help or contact a Poison Control Center right away.

If pregnant or breast-feeding, ask a health professional before use.

Do not use if tamper evident seal is broken or missing.

Keep out of reach of children. In case of overdose, get medical help or contact a Poison Control Center right away.

DIRECTIONS:

10 drops orally, 3 times a day. Consult a physician for use in children under 12 years of age.

INDICATIONS:

May help temporarily relieve symptoms associated with depression.

INACTIVE INGREDIENTS:

Demineralized Water, 25% Ethanol

QUESTIONS:

Distributed by:

SYNERGY FORMULAS, INC.

251 West Road

Campobello, SC 29322

PACKAGE LABEL DISPLAY:

Synergy Formulas

DEPRESSION COMPOSITION

HOMEOPATHIC

2 FL OZ (60 ml)